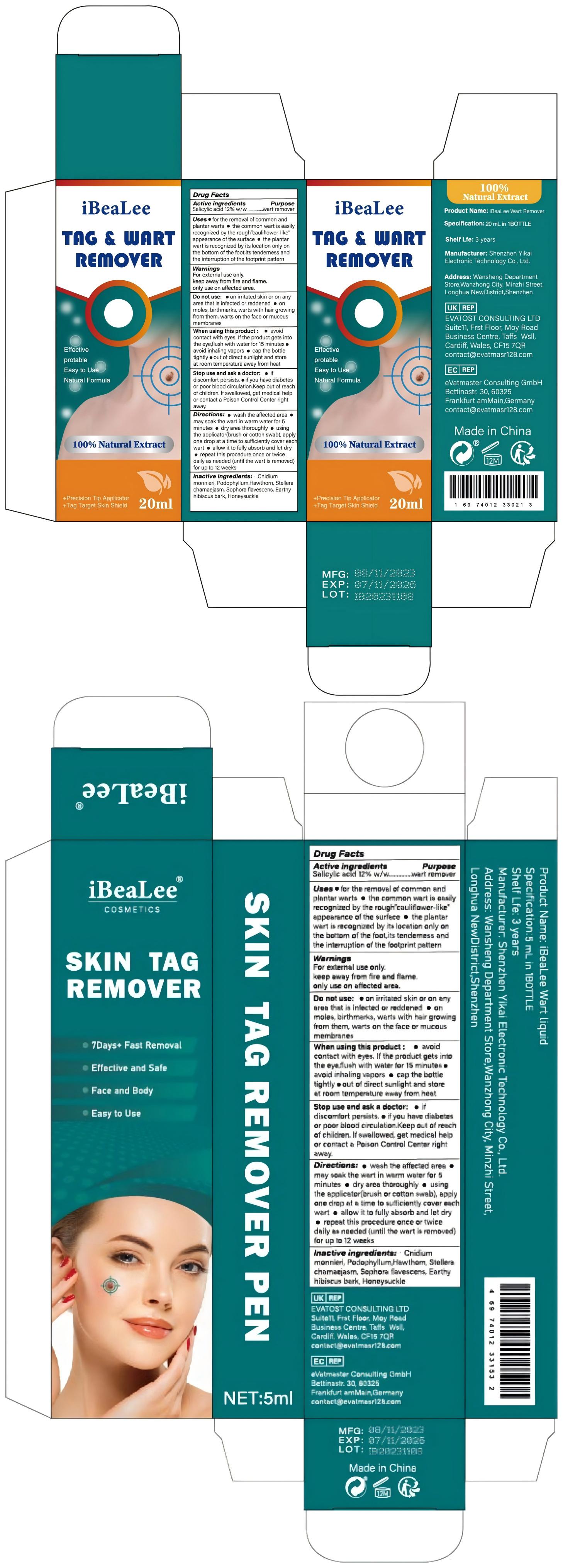 DRUG LABEL: iBeaLee Wart Remover
NDC: 83809-002 | Form: LIQUID
Manufacturer: Shenzhen Yikai Electronic Technology Co., Ltd.
Category: otc | Type: HUMAN OTC DRUG LABEL
Date: 20250211

ACTIVE INGREDIENTS: SALICYLIC ACID 12 g/100 mL
INACTIVE INGREDIENTS: PODOPHYLLUM; HIBISCUS SYRIACUS BARK; LONICERA HYPOGLAUCA FLOWER; CNIDIUM MONNIERI FRUIT OIL; HAWTHORN LEAF WITH FLOWER; SOPHORA FLAVESCENS ROOT; STELLERA CHAMAEJASME WHOLE

83809-002 V3

Active Ingredient

Salicylic acid 12%

Purpose

wart remover

Use

●for the removal of common and plantar warts

●the common wart is easily recognized by the rough”cauliflower-like” appearance of the surface

●the plantar wart is recognized by its location only on the bottom of the foot,its tenderness and the interruption of the footprint pattern

Warnings

For external use only.
keep away from fire and flame.
only use on affected area.

Do not use

●on irritated skin or on any area that is infected or reddened

●on moles, birthmarks, warts with hair growing from them, warts on the face or mucous membranes

When Using

● avoid contact with eyes. If the product gets into the eye,flush with water for 15 minutes
● avoid inhaling vapors

● cap the bottle tightly

●out of direct sunlight and store at room temperature away from heat

Stop Use

● if discomfort persists.

●if you have diabetes or poor blood circulation.Keep out of reach of children. lf swallowed, get medical help or contact a Poison Control Center right away.

Keep Oot Of Reach Of Children

Please store this product out of the reach of childre

Directions

● wash the affected area
●may soak the wart in warm water for 5 minutes · dry area thoroughly

● using the applicator(brush or cotton swab), apply one drop at a time to sufficiently cover each wart

● allow it to fully absorb and let dry
● repeat this procedure once or twice daily as needed (until the wart is removed) for up to 12 weeks

Inactive ingredients

Cnidium monnieri, Podophyllum,Hawthorn, Stellera chamaejasm, Sophora flavescens, Earthy hibiscus bark, Honeysuckle